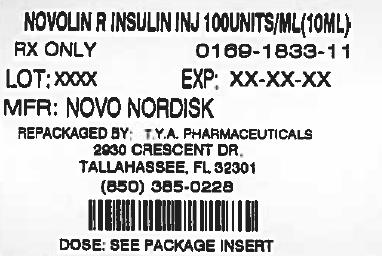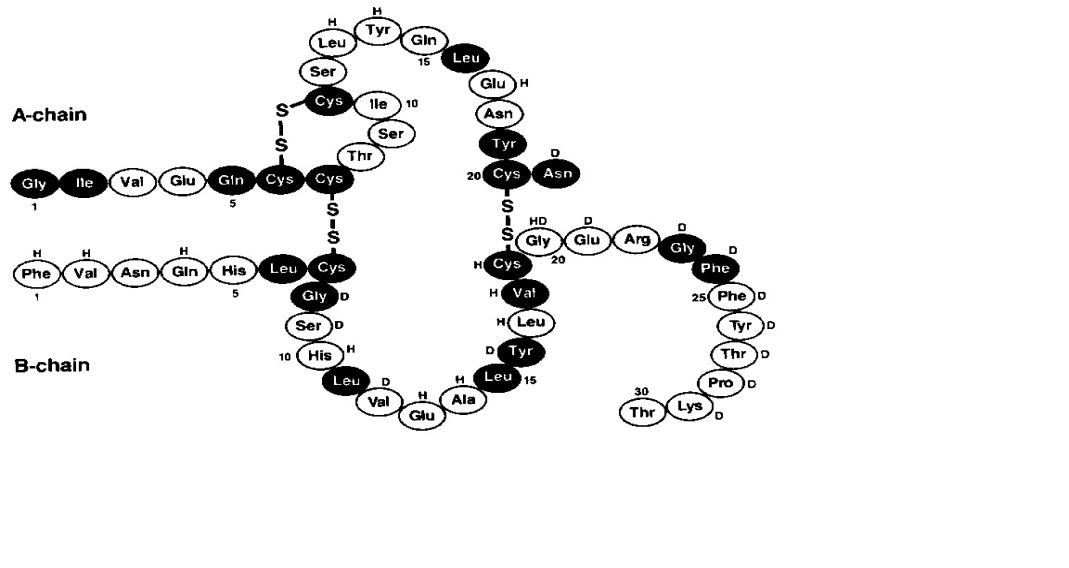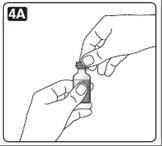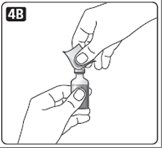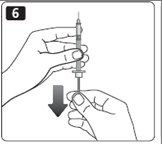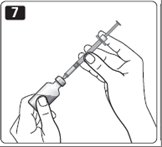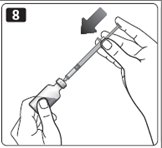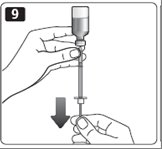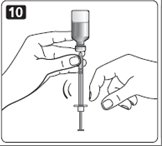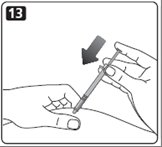 DRUG LABEL: Novolin
                                    
NDC: 64725-1833 | Form: INJECTION, SOLUTION
Manufacturer: TYA Pharmaceuticals
Category: otc | Type: HUMAN OTC DRUG LABEL
Date: 20130309

ACTIVE INGREDIENTS: INSULIN HUMAN 100 [iU]/1 mL
INACTIVE INGREDIENTS: ZINC CHLORIDE 7 ug/1 mL; GLYCERIN 16 mg/1 mL; METACRESOL 3 mg/1 mL; HYDROCHLORIC ACID; SODIUM HYDROXIDE; WATER

HIGHLIGHTS OF PRESCRIBING INFORMATION

These highlights do not include all the information needed to use Novolin R safely and effectively. See full prescribing information for Novolin R. Initial U.S. Approval: 1991
Novolin R (Regular, Human Insulin [rDNA origin] USP) solution for subcutaneous or intravenous use®

RECENT MAJOR CHANGES

Warnings and Precautions () 3/2013 5.9

1 INDICATIONS AND USAGE

Novolin R is a short-acting recombinant human insulin indicated to improve glycemic control in adults and children with diabetes mellitus (). 1

2 DOSAGE AND ADMINISTRATION

- The dosage and timing of Novolin R must be individualized (). 2.1
- Subcutaneous injection: Administer approximately 30 minutes prior to the start of a meal (). 2.2
- Intravenous use: Use at concentrations from 0.05 to 1.0 Unit/mL in infusion systems using polypropylene infusion bags. Novolin R is stable in 0.9% sodium chloride, 5% dextrose, or 10% dextrose with 40 mmol/L potassium chloride (). 2.3
- Use in pumps: Not recommended due to risk of precipitation (). 2.4

3 DOSAGE FORMS AND STRENGTHS

Novolin R, Regular, Human Insulin Injection (rDNA origin) USP, 100 units/mL (U-100), is supplied in 10 mL vials (). 3

4 CONTRAINDICATIONS

- Do not use during episodes of hypoglycemia (). 4
- Do not use in patients with hypersensitivity to Novolin R or one of its excipients (). 4

5 WARNINGS AND PRECAUTIONS

- Hypoglycemia: Most common adverse reaction of insulin therapy and may be life-threatening. Closely monitor blood glucose. Changes in insulin or dosage should be made cautiously and only under medical supervision (). 5.2
- Hypokalemia: Particularly when insulin is given intravenously or in settings of poor glycemic control. Use caution in patients predisposed to hypokalemia (). 5.3
- Renal or hepatic impairment: As with other insulins, the dose requirements for Novolin R may be reduced (). 5.5
- Allergic reactions: Severe, life-threatening, generalized allergy, including anaphylaxis, may occur (). 5.6
- Mixing: Do not mix Novolin R with any insulin for intravenous use. Do not mix with insulins other than NPH insulin for subcutaneous use (). 5.7
- Fluid retention and heart failure can occur with concomitant use of thiazolidinediones (TZDs), which are PPAR-gamma agonists, and insulin, including Novolin R (). 5.9

6 ADVERSE REACTIONS

Adverse reactions observed with Novolin R include hypoglycemia, allergic reactions, injection site reactions, lipodystrophy, weight gain and edema (). 6

To report SUSPECTED ADVERSE REACTIONS, contact Novo Nordisk Inc. at 1-800-727-6500 or FDA at 1-800-FDA-1088 orwww.fda.gov/medwatch.

7 DRUG INTERACTIONS

- Certain medications affect glucose metabolism and may require insulin dose adjustment and close monitoring (). 7
- The signs of hypoglycemia may be reduced or absent in patients taking anti-adrenergic medications (e.g., beta-blockers, clonidine, guanethidine, and reserpine) (). 7

FULL PRESCRIBING INFORMATION

1 INDICATIONS AND USAGE

1.1 Treatment of Diabetes Mellitus

Novolin R is indicated to improve glycemic control in adults and children with diabetes mellitus.

2 DOSAGE AND ADMINISTRATION

2.1 Dosing

The dosage and timing of Novolin R must be individualized. Blood glucose monitoring is essential for all patients receiving insulin therapy.

Total daily insulin requirements vary and are usually between 0.5 and 1.0 units/kg/day. Insulin requirements may be altered during stress, major illness, or with changes in exercise, meal patterns, or coadministered medications.

2.2 Subcutaneous Injection

Novolin R should generally be injected approximately 30 minutes prior to the start of a meal.

Novolin R given by subcutaneous injection should generally be used in regimens that include an intermediate or long-acting insulin . [see How Supplied/Storage and Handling (,)] 16.116.2

Novolin R should be administered by subcutaneous injection in the abdominal region, buttocks, thigh, or the upper arm. Subcutaneous injection into the abdominal wall is generally associated with faster absorption than other injection sites. Injection sites should be rotated within the same region to reduce the risk of lipodystrophy. Injection into a lifted skin fold minimizes the risk of intramuscular injection.

2.3 Intravenous Use

Novolin R can be administered intravenously under medical supervision for glycemic control, with close monitoring of blood glucose and potassium concentrations to avoid hypoglycemia and hypokalemia . [see Warnings and Precautions (,), How Supplied/Storage and Handling (,)] 5.25.316.116.2

Intravenous administration of insulin is commonly used in the treatment of diabetic ketoacidosis, peri-operative management of diabetes, and maintenance of glycemic control during labor in pregnant diabetic women. For intravenous use, Novolin R should be used at concentrations from 0.05 units/mL to 1.0 unit/mL in infusion systems using polypropylene infusion bags. Novolin R can be used with the following infusion fluids: 0.9% sodium chloride, 5% dextrose, or 10% dextrose with 40 mmol/L potassium chloride.

Parenteral drug products should be inspected visually for particulate matter and discoloration prior to administration, whenever solution and container permit. Never use Novolin R if it has become viscous or cloudy; use Novolin R only if it is clear and colorless. Vials should not be used if leakage is observed. Novolin R should not be used after the printed expiration date.

The onset of action of Novolin R, when administered intravenously, is more rapid in comparison to subcutaneous administration.

2.4 Use in Insulin Pumps

Use of Novolin R in insulin pumps is not recommended because of the risk of precipitation.

3 DOSAGE FORMS AND STRENGTHS

- Novolin R is available in 10 mL vials. The concentration of Novolin R is 100 USP units of human insulin (rDNA origin)/mL.

4 CONTRAINDICATIONS

Novolin R is contraindicated:

- During episodes of hypoglycemia
- In patients with hypersensitivity to Novolin R or one of its excipients

5 WARNINGS AND PRECAUTIONS

5.1 Administration

Subcutaneous injection of Novolin R should be followed by a meal. Patients should wait approximately 30 minutes after injection before starting the meal [ ]. see Dosage and Administration () 2.2

Any change of insulin dose should be made cautiously and only under medical supervision. Changing from one insulin product to another or changing the insulin strength may result in the need for a change in dosage. As with all insulin preparations, the time course of Novolin R action may vary in different individuals or at different times in the same individual and is dependent on many conditions, including dosage, the site of injection, local blood supply, temperature, and physical activity. Patients who change their level of physical activity or meal plan may require adjustment of insulin dosages. Insulin requirements may be altered during illness, emotional disturbances, or other stresses.

5.2 Hypoglycemia

Hypoglycemia is the most common adverse reaction of all insulin therapies, including Novolin R. Severe hypoglycemia may lead to unconsciousness, convulsions, temporary or permanent impairment of brain function or death. Severe hypoglycemia requiring the assistance of another person, parenteral glucose infusion, and glucagon administration has been observed in clinical trials with insulin, including trials with Novolin R.

The timing of hypoglycemia usually reflects the time-action profile of the administered insulin formulations [ ]. Other factors such as changes in food intake (e.g., amount of food or timing of meals), injection site, exercise, and concomitant medications may also alter the risk of hypoglycemia [ ]. As with all insulins, use caution in patients with hypoglycemia unawareness and in patients who may be predisposed to hypoglycemia (e.g., patients who are fasting or have erratic food intake, pediatric patients, and the elderly). The patient’s ability to concentrate and react may be impaired as a result of hypoglycemia. This may present a risk in situations where these abilities are especially important, such as driving or operating other machinery. see Clinical Pharmacology (,) 12.212.3 see Drug Interactions () 7

Rapid changes in serum glucose concentrations may induce symptoms of hypoglycemia in patients with diabetes, regardless of the glucose value. Early warning symptoms of hypoglycemia may be different or less pronounced under certain conditions, such as longstanding diabetes, diabetic neuropathy, use of medications such as beta-blockers, or intensified glycemic control [ ]. These situations may result in severe hypoglycemia (and, possibly, loss of consciousness) prior to the patient’s awareness of hypoglycemia. Intravenously administered insulin has a more rapid onset of action than subcutaneously administered insulin, requiring more close monitoring for hypoglycemia. see Drug Interactions () 7

5.3 Hypokalemia

All insulins, including Novolin R, cause a shift in potassium from the extracellular to intracellular space, possibly leading to hypokalemia that, if left untreated, may cause respiratory paralysis, ventricular arrhythmia, and death. Use caution in patients who may be at risk for hypokalemia (e.g., patients using potassium-lowering medications and patients taking medications sensitive to serum potassium concentrations). Monitor glucose and potassium frequently when Novolin R is administered intravenously.

5.4 Hyperglycemia, Diabetic Ketoacidosis, and Hyperosmolar Hyperglycemic Non-Ketotic Syndrome

Hyperglycemia, diabetic ketoacidosis, or hyperosmolar hyperglycemic non-ketotic syndrome may develop in patients who take less insulin than needed to control blood glucose. These conditions can be precipitated by illness, infection, dietary indiscretion, or omission or improper administration of the prescribed insulin dose.

5.5 Renal or Hepatic Impairment

As with other insulins, the dose requirements for Novolin R may be reduced in patients with renal or hepatic impairment.

5.6 Hypersensitivity and Allergic Reactions

- As with other insulins, patients may experience redness, swelling, or itching at the site of injection of Novolin R. These reactions usually resolve in a few days to a few weeks, but in some occasions, may require discontinuation of Novolin R. In some instances, these reactions may be related to factors other than insulin, such as irritants in a skin cleansing agent or poor injection technique. Localized reactions and generalized myalgias have been reported with the use of meta-cresol, which is an excipient in Novolin R. Local Reactions

- Severe, life-threatening, generalized allergy, including anaphylaxis may occur with any insulin, including Novolin R. Generalized allergy to insulin may manifest as a whole body rash (including pruritus), dyspnea, wheezing, hypotension tachycardia, or diaphoresis. Systemic Reactions,

5.7 Mixing of Insulins

If Novolin R is mixed with NPH human insulin, Novolin R should be drawn into the syringe first and the mixture should be injected immediately after mixing. Insulin mixtures should not be administered intravenously.

5.8 Antibody Production

Increases in titers of anti-insulin antibodies that react with human insulin have been observed in patients treated with Novolin R. Data from a 12-month controlled trial in patients with type 1 diabetes suggest that the increase in these antibodies is transient. The clinical significance of these antibodies is not known but does not appear to cause deterioration in glycemic control or necessitate increases in insulin dose.

5.9 Fluid retention and heart failure with concomitant use of PPAR-gamma agonists

Thiazolidinediones (TZDs), which are peroxisome proliferator-activated receptor (PPAR)-gamma agonists, can cause dose-related fluid retention, particularly when used in combination with insulin. Fluid retention may lead to or exacerbate heart failure. Patients treated with insulin, including NOVOLIN R, and a PPAR-gamma agonist should be observed for signs and symptoms of heart failure. If heart failure develops, it should be managed according to current standards of care, and discontinuation or dose reduction of the PPAR-gamma agonist must be considered.

6 ADVERSE REACTIONS

- Hypoglycemia

Hypoglycemia is the most commonly observed adverse reaction in patients using insulin, including Novolin R [ ]. see Warnings and Precautions () 5.2

- Insulin initiation and glucose control intensification

Intensification or rapid improvement in glucose control has been associated with a transitory, reversible ophthalmologic refraction disorder, worsening of diabetic retinopathy, and acute painful peripheral neuropathy. Over the long-term, improved glycemic control decreases the risk of diabetic retinopathy and neuropathy.

- Lipodystrophy

Long-term use of insulin, including Novolin R, can cause lipodystrophy at the site of repeated insulin injections. Lipodystrophy includes lipohypertrophy (thickening of adipose tissue) and lipoatrophy (thinning of adipose tissue), and may affect insulin absorption. Rotate insulin injection sites within the same region to reduce the risk of lipodystrophy.

- Weight gain

Weight gain can occur with insulin therapies, including Novolin R, and has been attributed to the anabolic effects of insulin and the decrease in glucosuria.

- Peripheral edema

Insulin may cause sodium retention and edema, particularly if previously poor metabolic control is improved by intensified insulin therapy. These symptoms are usually transitory.

- Allergic reactions

As with other insulins, Novolin R can cause injection site reactions. Severe, life-threatening, generalized allergy, including anaphylaxis may occur with any insulin, including Novolin R [ ]. see Warnings and Precautions () 5.6

Clinical Trial Experience

Because clinical trials are conducted under widely varying designs, the adverse reaction rates reported in one clinical trial may not be easily compared to those rates reported in another clinical trial, and may not reflect the rates actually observed in clinical practice.

Adults with type 1 or type 2 diabetes

The incidence of adverse reactions during clinical trials comparing Novolin R and insulin aspart in adults with type 1 diabetes mellitus and type 2 diabetes mellitus are listed in the tables below.

Table 1: Adverse Reactions in a 24-Week Trial Comparing Novolin R and Insulin Aspart in Adults with Type 1 Diabetes Mellitus Also Treated with NPH Insulin (adverse reactions with an incidence ≥ 5% in the Novolin R treatment group are listed)

 | Novolin R + NPH N= 286 | Insulin aspart + NPH N=596
 | % | %
Hypoglycemia [Hypoglycemia was defined as an episode of blood glucose concentration <45 mg/dL, with or without symptoms.] | 72 | 75

Table 2: Adverse Reactions in a 24-Week Trial Comparing Novolin R and Insulin Aspart in Adults with Type 2 Diabetes Mellitus Also Treated with NPH Insulin (adverse reactions with an incidence ≥ 5% in the Novolin R treatment group are listed)

 | Novolin R + NPH N= 91 | Insulin aspart + NPH N= 91
 | (%) | (%)
Hypoglycemia [Hypoglycemia was defined as an episode of blood glucose concentration <45 mg/dL, with or without symptoms.] | 36 | 27

Children and adolescents with type 1 diabetes

The incidence of adverse reactions during a 24-week clinical trial comparing Novolin R and insulin aspart in children and adolescents with type 1 diabetes mellitus are listed in the table below.

Table 3: Adverse Reactions in a 24-Week Trial Comparing Novolin R and Insulin Aspart in Children and Adolescents with Type 1 Diabetes Mellitus Also Treated with NPH Insulin (adverse reactions with an incidence ≥5% in the Novolin R treatment group are listed)

 | Novolin R + NPH N= 96 | Insulin aspart + NPH N= 187
 | (%) | (%)
Hypoglycemia [Hypoglycemia was defined as an episode of blood glucose concentration <50 mg/dL, with or without symptoms.] | 85 | 79
Injection site hypertrophy | 8 | 8

Severe Hypoglycemia

Hypoglycemia is the most commonly observed adverse reaction in patients using insulin, including Novolin R Tables 4 and 5 summarize the incidence of severe hypoglycemia in the Novolin R clinical trials. Severe hypoglycemia was defined as hypoglycemia associated with central nervous system symptoms and requiring intervention of another person or hospitalization. The rates of severe hypoglycemia in the Novolin R clinical trials (see Section 14 for a description of the study designs) were comparable for all treatment regimens (see Tables 4 and 5). [See Warnings and Precautions ()]. 5.3

Table 4: Severe Hypoglycemia in Patients with Type 1 Diabetes

 | Type 1 Diabetes; Adults; 24 weeks in combination with NPH insulin |  | Type 1 Diabetes; Children and Adolescents; (age 6-18); 24 weeks in combination with NPH insulin |  | Type 1 Diabetes; Children; (age 2-6); 24 weeks in combination with NPH insulin
 | Novolin R | Insulin aspart | Novolin R | Insulin aspart | Novolin R | Insulin aspart
Percent of patients (n/total N) | 19; (55/286) | 18; (105/596) | 9; (9/96) | 6; (11/187) | 12; (3/25) | 8; (2/26)
Event/patient/; year | 1.1 | 0.9 | 0.3 | 0.2 | 0.5 | 0.3

Table 5: Severe Hypoglycemia in Patients with Type 2 Diabetes

 | Type 2 Diabetes; Adults; 24 weeks in combination with; NPH insulin
 | Novolin R | Insulin aspart
Percent of patients; (n/total N) | 5; (5/91) | 10; (9/91)
Event/patient/; year | 0.2 | 0.3

7 DRUG INTERACTIONS

A number of medications affect glucose metabolism that may require insulin dose adjustment and particularly close monitoring for hypoglycemia or worsening glycemic control.

- The following are examples of medications that may increase the blood glucose-lowering effect of insulin and increase susceptibility to hypoglycemia: oral antidiabetic medications, pramlintide acetate, angiotensin converting enzyme (ACE) inhibitors, disopyramide, fibrates, fluoxetine, monoamine oxidase (MAO) inhibitors, propoxyphene, salicylates, somatostatin analogs (e.g., octreotide), and sulfonamide antibiotics.
- The following are examples of medications that may reduce the blood glucose-lowering effect of insulin, leading to worsening of glycemic control: corticosteroids, niacin, danazol, diuretics, sympathomimetic agents (e.g., epinephrine, salbutamol, terbutaline), isoniazid, phenothiazine derivatives, somatropin, thyroid hormones, estrogens, progestogens (e.g., in oral contraceptives), and atypical antipsychotics.
- Beta-blockers, clonidine, and lithium salts may either potentiate or weaken the blood glucose-lowering effect of insulin.
- Alcohol can increase susceptibility to hypoglycemia.
- Pentamidine may cause hypoglycemia, which may sometimes be followed by hyperglycemia.
- The signs of hypoglycemia may be reduced or absent in patients taking sympatholytic medications such as beta-blockers, clonidine, guanethidine, and reserpine.

8 USE IN SPECIFIC POPULATIONS

8.1 Pregnancy

Pregnancy Category B: All pregnancies have a background risk of birth defects, loss, or other adverse outcome regardless of drug exposure. This background risk is increased in pregnancies complicated by hyperglycemia and may be decreased with good glycemic control. It is essential for patients with diabetes or a history of gestational diabetes to maintain good glycemic control before conception and throughout pregnancy. Insulin requirements may decrease during the first trimester, generally increase during the second and third trimesters, and rapidly decline after delivery. Careful monitoring of glucose control is important during pregnancy in patients with diabetes. Therefore, women should be advised to tell their healthcare provider if they intend to become, or if they become, pregnant while taking Novolin R.

No reproductive toxicity studies have been performed with Novolin R.

8.3 Nursing Mothers

It is unknown whether Novolin R is excreted in breast milk. Small amounts of human insulin are secreted into breast milk, the significance of which is not known. Use of Novolin R is compatible with breastfeeding, but insulin doses may need to be adjusted because lactation can reduce insulin requirements.

8.4 Pediatric Use

The safety and effectiveness of subcutaneous injections of Novolin R have been established in pediatric patients (ages 2 to18 years) with type 1 diabetes . Novolin R has not been studied in pediatric patients younger than 2 years of age. Novolin R has not been studied in pediatric patients with type 2 diabetes. [see Clinical Studies ()] 14.3

In general, pediatric patients with type 1 diabetes are more susceptible to hypoglycemia than adult patients with type 1 diabetes. As in adults, the dosage of Novolin R must be individualized in pediatric patients based on metabolic needs and frequent monitoring of blood glucose . [see Dosage and Administration () and Warnings and Precautions ()] 2.15.2

8.5 Geriatric Use

In 3 controlled clinical trials 18 of 1285 patients (1.4%) with type 1 diabetes treated with Novolin R and insulin aspart were ≥65 years of age. In 4 controlled clinical trials 151 of 635 patients (24%) with type 2 diabetes were ≥65 years of age. Therefore, conclusions are limited regarding the efficacy and safety of Novolin R in patients ≥65 years of age, particularly in patients with type 1 diabetes. Pharmacokinetic/pharmacodynamic studies to assess the effect of age on Novolin R have not been performed.

Use caution in patients with advanced age, due to the potential for decreased renal function in this population . [see Warnings and Precautions (and)] 5.25.5

10 OVERDOSAGE

Excess insulin administration may cause hypoglycemia and, particularly when given intravenously, hypokalemia. Mild episodes of hypoglycemia usually can be treated with oral glucose. Adjustments in drug dosage, meal patterns, or exercise may be needed. More severe episodes with coma, seizure, or neurologic impairment can be treated with intramuscular or subcutaneous glucagon or intravenous glucose. Sustained carbohydrate intake and observation may be necessary because hypoglycemia may recur after apparent clinical recovery. Hypokalemia must be corrected appropriately. [ see Warnings and Precautions (,)] 5.25.3

11 DESCRIPTION

Novolin R (Regular Human Insulin Injection [Recombinant DNA origin] United States Pharmacopeia) is a polypeptide hormone structurally identical to native human insulin and is produced by recombinant DNA technology, utilizing (baker’s yeast) as the production organism. Novolin R has the empirical formula C H N O S and a molecular weight of 5808. Saccharomyces cerevisiae25738365776

Figure 1: Structural formula of Novolin R

Novolin R is a sterile, clear, aqueous, and colorless solution that contains human insulin (rDNA origin) 100 units/mL, glycerol 16 mg/mL, metacresol 3 mg/mL, zinc chloride approximately 7 mcg/mL and water for injection. The pH is adjusted to 7.4. Hydrochloric acid 2N or sodium hydroxide 2N may be added to adjust pH. Novolin R vials are latex-free.

12 CLINICAL PHARMACOLOGY

12.1 Mechanism of Action

The primary activity of Novolin R is the regulation of glucose metabolism. Insulins, including Novolin R, bind to insulin receptors on muscle and adipocytes and lower blood glucose by facilitating the cellular uptake of glucose and simultaneously inhibiting the output of glucose from the liver.

12.2 Pharmacodynamics

Novolin R is a short-acting insulin. When injected subcutaneously, the glucose-lowering effect of Novolin R begins approximately 30 minutes post-dose, is maximal between 1.5 and 3.5 hours post-dose and terminates approximately 8 hours post-dose. The onset of action of Novolin R, when administered intravenously, is more rapid in comparison to the subcutaneous administration. When injected subcutaneously, Novolin R has a slower onset of action and longer duration of action compared to the rapid-acting insulin analogs.

12.3 Pharmacokinetics

After single subcutaneous administration of 0.1 unit/kg of Novolin R to healthy subjects, peak insulin concentrations occurred between 1.5 to 2.5 hours post-dose. On average, insulin concentrations returned to baseline at around 5 hours post-dose.

The effects of sex, age, obesity, ethnic origin, renal and hepatic impairment, pregnancy, and smoking, on the pharmacodynamics and pharmacokinetics of Novolin R have not been studied.

13 NONCLINICAL TOXICOLOGY

13.1 Carcinogenesis, Mutagenesis, Impairment of Fertility

Standard 2-year carcinogenicity studies in animals have not been performed to evaluate the carcinogenic potential of Novolin R.

Novolin R is not mutagenic in the following tests: The chromosomal aberration assay in human lymphocytes, the micronucleus assay in mouse polychromatic erythrocytes, and the mutation frequency assay in Chinese hamster cells. in vitro

Standard reproduction and teratology studies in animals, including fertility assessments have not been conducted with Novolin R.

14 CLINICAL STUDIES

Please see for information on the pharmacokinetics and pharmacodynamics of Novolin R. Section 12 CLINICAL PHARMACOLOGY

14.1 Type 1 diabetes mellitus (adults)

Two six‑month, open‑label, active-controlled studies were conducted to compare the safety and efficacy of Novolin R and insulin aspart in adults with type 1 diabetes. Insulin aspart was administered by subcutaneous injection immediately prior to meals and Novolin R was administered by subcutaneous injection 30 minutes before meals. Both treatment groups also received subcutaneous injections of NPH insulin in either single or divided daily doses. Because the two study designs and results were similar, data are shown for only one study (see Table 6)

Table 6: Subcutaneous Novolin R Administration in Type 1 Diabetes (24 weeks; N=882)

 | Novolin R + NPH; N=286 | Insulin aspart + NPH N=596
Baseline HbA1c (%) [Values are Mean ± SD] | 8.0 ± 1.2 | 7.9 ±1.1
Change from Baseline HbA (%)1c | 0.0 ± 0.8 | -0.1 ± 0.8
Treatment Difference in HbA , Mean (95% confidence interval)1c; Novolin R – insulin aspart group | 0.2 [0.1; 0.3]
Baseline, total insulin dose (units/kg/day) | 0.7 ± 0.2 | 0.7 ± 0.2
End-of-Study, total insulin dose (units/kg/day) | 0.7 ± 0.2 | 0.7 ± 0.2
Baseline body weight (kg); Weight Change from baseline (kg) | 75.9 ± 13.1; 0.9 ± 2.9 | 75.3 ± 14.5; 0.5 ± 3.3

14.2 Type 2 diabetes mellitus (adults)

A six‑month, open‑label, active-controlled study was conducted to compare the safety and efficacy of Novolin R and insulin aspart in adults with type 2 diabetes (Table 7). Insulin aspart was administered by subcutaneous injection immediately prior to meals and Novolin R was administered by subcutaneous injection 30 minutes before meals. Both treatment groups also received subcutaneous injections of NPH insulin in either single or divided daily doses.

Table 7: Subcutaneous Novolin R Administration in Type 2 Diabetes (24 weeks; N=182)

 | Novolin R + NPH; N = 91 | Insulin aspart + NPH; N = 91
Baseline HbA (%)1c [Values are Mean ± SD] | 7.8 ± 1.1 | 8.1 ± 1.2
Change from Baseline HbA (%)1c | -0.1 ± 0.8 | -0.3 ± 1.0
Treatment Difference in HbA Mean (95% confidence interval)1c,; Novolin R – insulin aspart group | 0.1 [-0.1; 0.4]
Baseline, total insulin dose (units/kg/day) | 0.6 ± 0.3 | 0.6 ± 0.3
End-of-Study, total insulin dose (units/kg/day) | 0.7 ± 0.3 | 0.7 ± 0.3
Baseline body weight (kg); Weight Change from baseline (kg) | 85.8 ± 14.8; 0.4 ± 3.1 | 88.4± 13.3; 1.2± 3.0

14.3 Type 1 diabetes mellitus (children and adolescents)

A six‑month, open‑label, active-controlled study was conducted to compare the safety and efficacy of Novolin R and insulin aspart in children and adolescents aged 6-18 years with type 1 diabetes (Table 8). Insulin aspart was administered by subcutaneous injection immediately prior to meals and Novolin R was administered by subcutaneous injection 30 minutes before meals. Both treatment groups also received subcutaneous injections of NPH insulin.

Table 8: Subcutaneous Novolin R Administration in Children and Adolescents with Type 1 Diabetes (24 weeks; N=283)

 | Novolin R + NPH; N=96 | Insulin aspart + NPH; N=187
Baseline HbA (%)1c [Values are Mean ± SD] | 8.3 ± 1.3 | 8.3 ± 1.2
Change from Baseline HbA (%)1c | 0.1 ± 1.1 | 0.1 ± 1.0
Treatment Difference in HbA Mean (95% confidence interval)1c,; Novolin R – insulin aspart group [The treatment difference and corresponding 95% confidence interval is based on the Analysis of Covariance Model] | 0.2 [-0.1; 0.5]
Baseline, total insulin dose (units/kg/day) | 1.0 ± 0.4 | 1.0 ± 0.3
End-of-Study, total insulin dose (units/kg/day) | 1.2 ± 0.4 | 1.2 ± 0.4
Diabetic ketoacidosis n (%) | 2 (2%) | 10 (5%)
Baseline body weight (kg); Weight Change from baseline (kg) | 48.7 ± 15.8; 2.4 ± 2.6 | 50.6 ± 19.6; 2.7 ± 3.5

Novolin R and insulin aspart have also been compared in an open-label, randomized, crossover trial in 26 children with type 1 diabetes aged 2-6 years. Patients received each treatment for 12 weeks. Insulin aspart was administered by subcutaneous injection immediately prior to meals and Novolin R was administered by subcutaneous injection 30 minutes before meals. Both treatment groups also received subcutaneous injections of NPH insulin. In this study, the mean baseline HbA was 7.8%.1c

The estimated HbA at end of treatment was 7.6% with Novolin R and 7.7% with insulin aspart.1c

16 HOW SUPPLIED/STORAGE AND HANDLING

NDC:64725-1833-1 in a VIAL of 10 INJECTION, SOLUTIONS

16.1 How Supplied

Novolin R is available in 10 mL vials (NDC 0169-1833-11 and ReliOn brand NDC 0169-1833-02). The concentration of Novolin R is 100 USP units of human insulin (rDNA origin)/mL. One vial is provided in each sale pack.®

16.2 Recommended Storage

Unopened Novolin R vials should be stored in the refrigerator (36° - 46°F [2° - 8°C]). If carried as a spare or if refrigeration is not possible, unopened Novolin R vials can be kept at room temperature provided they are kept as cool as possible (not above 77 F [25 C]). If kept at room temperature, Novolin R vials must be discarded after 42 days even if they are unopened.oo

In addition, unopened Novolin R vials should be kept in their cartons so that they will stay clean and protected from light. They should not be exposed to heat or light. Do not freeze and do not use Novolin R if it has been frozen.

An opened (In use) Novolin R vial can be kept at room temperature provided it is kept as cool as possible (not above 77 F [25 C]) and away from heat or light. Do not refrigerate after first use.oo

Unopened and opened (In use) Novolin R vials must be discarded 42 days after they are first kept out of the refrigerator, even if they still contain Novolin R insulin.

Table 9: Storage Conditions for Novolin R vials

Unopened; (Refrigerated) | Unopened; (Room Temperature up to 77 F [25 C])oo | Opened (In use); (Room Temperature up to 77 F [25 C])oo
Until expiration date | 42 days [The total time allowed at room temperature (up to 25 C) is 42 days regardless of whether the product is unopened or opened (In use)o] | 42 days

Infusion bags prepared as indicated under are stable at room temperature for 24 hours. A certain amount of insulin will be initially adsorbed to the material of the infusion bag. DOSAGE AND ADMINISTRATION () 2.3

Always remove the needle after each injection. Always use a new disposable syringe and needle for each injection to prevent contamination.

Never use insulin after the expiry date which is printed on the label and carton.

17 PATIENT COUNSELING INFORMATION

See FDA-Approved Patient Labeling (Patient Information and Instructions for Use)

17.1 Instructions for All Patients

Maintenance of normal or near-normal glucose control is a treatment goal in diabetes mellitus and has been associated with a reduction in some diabetic complications. Patients should be informed about potential risks and benefits of Novolin R therapy including possible adverse reactions. Patients should also be offered continued education and advice on insulin therapies, injection technique, life-style management, regular glucose monitoring, periodic glycosylated hemoglobin testing, recognition and management of hypo- and hyperglycemia, adherence to meal planning, complications of insulin therapy, timing of dose, instruction in the use of injection devices, and proper storage of insulin. Patients should be informed that frequent, patient-performed blood glucose measurements are needed to achieve optimal glycemic control and avoid both hyper- and hypoglycemia.

The patient’s ability to concentrate and react may be impaired as a result of hypoglycemia. This may present a risk in situations where these abilities are especially important, such as driving or operating other machinery. Patients who have frequent hypoglycemia or reduced or absent warning signs of hypoglycemia should be advised to use caution when driving or operating machinery. Female patients should be advised to tell their physician if they intend to become, or if they become pregnant.

Patients should be instructed to always carefully check that they are administering the correct insulin to avoid medication errors between Novolin R and other insulins. Patients should check the label for the drug name Novolin R, the enlarged R letter, and the blue horizontal bar. If a prescription for Novolin R is needed, it should be written clearly to avoid confusion with other insulin products.

Novolin is a registered trademark of Novo Nordisk A/S.®

ReliOn is a registered trademark of Wal-Mart Stores, Inc. and is used under license by Novo Nordisk Inc.®

© 2002-2013 Novo Nordisk

Manufactured by:

Novo Nordisk A/S

DK-2880 Bagsvaerd, Denmark

ReliOn brand manufactured by:®

Novo Nordisk A/S

DK-2880 Bagsvaerd, Denmark

For Wal-Mart Stores Inc.

For information about Novolin R contact:

Novo Nordisk Inc.

800 Scudders Mill Road

Plainsboro, New Jersey 08536

www.novonordisk-us.com

1-800-727-6500

PATIENT PACKAGE INSERT

Patient Information

NOVOLIN R (NO-voe-lin)®

(Regular, Human Insulin Injection [recombinant DNA origin] USP)

solution for subcutaneous injection

Read the Patient Information leaflet that comes with Novolin R before you start taking it and each time you get a refill. There may be new information. This leaflet does not take the place of talking with your healthcare provider about your diabetes or your treatment. Make sure you know how to manage your diabetes. Ask your healthcare provider if you have any questions about managing your diabetes.®

What is Novolin R?®

Novolin R is a man-made insulin (recombinant DNA origin) that is used to control high blood sugar in adults and children with diabetes mellitus.®

Who should not use Novolin R?®

Do not take Novolin R if:®

- Your blood sugar is too low (hypoglycemia). After treating your low blood sugar, follow your healthcare provider’s instructions on the use of Novolin R. ®
- You are allergic to any of the ingredients in Novolin R. See the end of this leaflet for a complete list of ingredients in Novolin R. Check with your healthcare provider if you are not sure. ®®

What should I tell my healthcare provider before taking Novolin R?®

Before you take Novolin R, tell your healthcare providers if you:®

- have liver or kidney problems.
- take any other medicines, especially ones commonly called TZDs (thiazolidinediones).
- If you have heart failure, it may get worse while you take TZDs with Novolin R. have heart failure or other heart problems.®
- Medical conditions can affect your insulin needs and your dose of Novolin R. have any other medical conditions.®
- Talk to your healthcare provider if you are pregnant or plan to become pregnant. You and your healthcare provider should talk about the best way to manage your diabetes while you are pregnant. are pregnant or plan to become pregnant.
- It is not known if Novolin R passes into breast milk. You and your healthcare provider should decide if you will take Novolin R while you breast-feed. are breast-feeding or plan to breast-feed.®®

including prescription and nonprescription medicines, vitamins and herbal supplements. Novolin R may affect the way Tell your healthcare provider about all of the medicines you take,®

other medicines work, and other medicines may affect how Novolin R works.®

Keep a list of your medicines with you to show all your Know the medicines you take.

healthcare providers and pharmacist when you get a new medicine.

How should I take Novolin R?®

- Novolin R comes in 10 mL vials for use with a syringe. ®
- Take Novolin R exactly as prescribed.®
- Your healthcare provider will tell you how much Novolin R to take and when to take it. ®
- Do not make any changes to your dose or type of insulin unless you are told to do so by your healthcare provider.
- The effects of Novolin R usually start working within about 30 minutes after your injection and usually lasts for up to 8 hours. ®
- your total dose of insulin, your dose of Novolin R, your dose of longer-acting insulin, or the number of injections of insulin you use. While using Novolin R your healthcare provider may change®®
- with any insulins other than NPH in the same syringe. Do not mix Novolin R®
- Novolin R may affect your blood sugar levels faster if you inject it into the skin of your abdomen (stomach area). Inject Novolin R under your skin (subcutaneously) of your abdomen (stomach area), upper arms, buttocks or upper legs.®® Never inject Novolin R into a vein or into a muscle.®
- Do not use Novolin R in an insulin pump.®
- Change (rotate) your injection site within the chosen area (for example, stomach or upper arm) with each dose. Do not inject into the same spot for each injection.
- Talk to your healthcare provider if you have any questions. Your healthcare provider should show you how to inject Novolin R before you start taking it. Read the instructions for use that comes with your Novolin R.®®
- You can treat mild low blood sugar (hypoglycemia) by drinking or eating something sugary right away (fruit juice, sugar candies, or glucose tablets). It is important to treat low blood sugar (hypoglycemia) right away because it could get worse and could lead to passing out (loss of consciousness), seizures and death. If you take too much Novolin R, your blood sugar may fall too low (hypoglycemia).®
- If high blood sugar (hyperglycemia) is not treated it can lead to serious problems, like loss of consciousness (passing out), coma or even death. Follow your healthcare provider’s instructions for treating high blood sugar. Know your symptoms of high blood sugar which may include: If you forget to take your dose of Novolin R, your blood sugar may go too high (hyperglycemia).®
  ∘ increased thirst
  ∘ frequent urination and dehydration
  ∘ confusion or drowsiness
  ∘ loss of appetite
  ∘ fruity smell on breath
  ∘ high amounts of sugar and ketones in your urine
  ∘ nausea, vomiting (throwing up) or stomach pain
  ∘ a hard time breathing
- Do not share needles or syringes with others. You may give an infection to them or get an infection from them.
- Ask your healthcare provider what your blood sugars should be and how often you should check your blood sugar levels for hypoglycemia (too low blood sugar) and hyperglycemia (too high blood sugar). Check your blood sugar levels.

Your insulin dosage may need to change because of:

- illness
- stress
- other medicines you take
- change in diet
- change in physical activity or exercise
- surgery

See the end of this patient information for instructions about preparing and giving the injection.

What should I avoid while taking Novolin R?®

- Alcohol may affect your blood sugar when you take Novolin R. This could lead to blood sugar that is too low (hypoglycemia). Drinking alcohol.®
  ∘ You may have trouble paying attention or reacting if you have low blood sugar (hypoglycemia). Be careful when you drive a car or operate machinery. Ask your healthcare provider if it is alright for you to drive if you often have: Driving and operating machinery.
  ∘ low blood sugar
  ∘ decreased or no warning signs of low blood sugar

What are the possible side effects of Novolin R?®

Novolin R may cause serious side effects, including:®

- Low blood sugar (hypoglycemia).

The general symptoms of low blood sugar (hypoglycemia) may be one or more of the following:

- sweating
- dizziness or lightheadedness
- shakiness
- hunger
- fast heart beat
- tingling in your hands, feet, lips or tongue
- trouble concentrating or confusion
- blurred vision
- slurred speech
- anxiety, irritability or mood changes
- headache

Very low blood sugar (hypoglycemia) can cause loss of consciousness (passing out), seizures, temporary or permanent brain problems or death.

Talk to your healthcare provider about how to tell if you have low blood sugar and what to do if this happens while taking Novolin R. Know your symptoms of low blood sugar. Follow your healthcare provider’s instructions for treating low blood sugar. ®

Talk to your healthcare provider if low blood sugar is a problem for you. Your dose of Novolin R may need to be changed. ®

- A decrease of potassium in your blood can cause breathing problems, a change in your heartbeat and death. Low blood potassium (hypokalemia).
- Serious allergic reaction (whole body reaction). You can have a serious allergic reaction that may be life-threatening. Get medical help right away if you have any of these symptoms of an allergic reaction:
  - a rash over your body
  - have trouble breathing
  - a fast heartbeat
  - sweating
  - feel faint
- Swelling of your hands and feet.
- Taking certain diabetes pills called thiazolidinediones or “TZDs” with Novolin R may cause heart failure in some people. This can happen even if you have never had heart failure or heart problems before. If you already have heart failure it may get worse while you take TZDs with Novolin R . Your healthcare provider should monitor you closely while you are taking TZDs with Novolin R. Tell your healthcare provider if you have any new or worse symptoms of heart failure including: Heart Failure.®®®
  - shortness of breath
- swelling of your ankles or feet
- sudden weight gain
Treatment with TZDs and Novolin R may need to be adjusted or stopped by your healthcare provider if you have new or worse heart failure. ®

Other side effects of Novolin R may include:®

- You may get redness, swelling, and itching at the injection site. If you keep having skin reactions, or they are serious, talk to your healthcare provider. You may need to stop using Novolin R and use a different insulin. Do not inject insulin into skin that is red, swollen, or itchy. Reactions at the injection site (local allergic reaction).®
- The fatty tissue under the skin may shrink (lipoatrophy) or thicken (lipohypertrophy) at the injection site. Change (rotate) the site where you inject your insulin to help reduce the chance of developing these skin changes. Do not inject insulin into this type of skin. Changes at the injection site (lipodystrophy).
- Weight gain.
- Swelling of your arms and legs.

Tell your healthcare provider if you have any side effect that bothers you or that does not go away.

These are not all of the possible side effects from Novolin R. Ask your healthcare provider or pharmacist for more information.®

Call your doctor for medical advice about side effects. You may report side effects to FDA at 1-800-FDA-1088.

How should I store Novolin R?®

Unopened Novolin R:®

- Unopened vials can be used until the expiration date on the Novolin R label, if the medicine has been stored in a refrigerator. Unopened Novolin R should be kept in the refrigerator between 36°F to 46°F (2° to 8°C).®®
- If refrigeration is not possible or if you want to carry a spare Novolin R vial you can keep the unopened vial at room temperature for up to 42 days, as long as it is kept at or below 77°F (25°C). Throw away the vial 42 days after it is first kept out of the refrigerator, even if the vial is unopened. ®
- Do not freeze. Do not use Novolin R if it has been frozen. ®
- Keep unopened Novolin R in the carton to protect it from light. ®

Novolin R in use:®

- Keep at room temperature below 77°F (25°C).
- Keep vials away from heat or light.
- Do not refrigerate an opened vial.
- Throw away the vial 42 days after it is first kept out of the refrigerator, even if there is insulin left in the vial.

Never use insulin after the expiration date which is printed on the label and carton.

General information about Novolin R®

Medicines are sometimes prescribed for conditions that are not mentioned in the patient leaflet. Do not use Novolin R for a condition for which it was not prescribed. Do not give Novolin R to other people, even if they have the same symptoms you have. It may harm them.®®

This leaflet summarizes the most important information about Novolin R. If you would like more information about Novolin R or diabetes, talk with your healthcare provider. You can ask your healthcare provider or pharmacist for information about Novolin R that is written for healthcare professionals.®®®

For more information about Novolin R, call 1-800-727-6500 or go to .® www.novonordisk-us.com

What are the ingredients in Novolin R?®

Regular Human Insulin Injection (recombinant DNA origin) USP. Active ingredient:

glycerol, metacresol, zinc chloride, water for injection, hydrochloric acid and sodium hydroxide may be added. Inactive ingredients:

All Novolin R vials are latex-free.®

This Patient Information has been approved by the U.S. Food and Drug Administration.

Date of issue: 03/2013

Novolin is a registered trademark of Novo Nordisk A/S.®

© 2002-2013 Novo Nordisk

Manufactured by:

Novo Nordisk A/S

DK-2880 Bagsvaerd, Denmark

For information about Novolin R contact:®

Novo Nordisk Inc.

800 Scudders Mill Road

Plainsboro, New Jersey 08536

1-800-727-6500

www.novonordisk-us.com

Patient Instructions for Use

Novolin R 10 mL vial (100 Units/mL, U-100)®

Please read the following Instructions for Use carefully before using your Novolin R 10 mL vial and®

each time you get a refill. You should read the instructions in this manual even if you have used an

insulin 10 mL vial before. There may be new information.

Before starting, gather all of the supplies that you will need to use for preparing and giving your insulin

injection.

Never re-use syringes and needles.

How should I use the Novolin R vial?

1. Check to make sure that you have the correct type of insulin. This is especially important if you use different types of insulin.

2. Look at the vial and the insulin. The insulin should be clear and colorless. The tamper-resistant cap should be in place before the first use. If the cap had been removed before your first use of the vial, or if the insulin is cloudy, colored, or contains any particles, do not use it and call Novo Nordisk at 1-800-727-6500.

3. Wash your hands with soap and water. Clean your injection site with an alcohol swab and let the injection site dry before you inject. Talk with your healthcare provider about how to rotate injection sites and how to give an injection.

4. If you are using a new vial, pull off the tamper-resistant cap.

Wipe the rubber stopper with an alcohol swab.

5. Do not roll or shake the vial. Shaking right before the dose is drawn into the syringe may cause bubbles or foam. This can cause you to draw up the wrong dose of insulin.

6. Pull back the plunger on the syringe until the black tip reaches the marking for the number of units you will inject.

7. Push the needle through the rubber stopper of the vial.

8. Push the plunger all the way in to force air into the vial.

9. Turn the vial and syringe upside down and slowly pull the plunger back to a few units beyond the correct dose.

10. If there are any air bubbles, tap the syringe gently with your finger to raise the air bubbles to the top. Then slowly push the plunger to the marking for your correct dose. This process should move any air bubbles present in the syringe back into the vial.

11. Check to make sure you have the right dose of Novolin R in the syringe.

12. Pull the syringe out of the vial’s rubber stopper.

13. Your healthcare provider should tell you if you need to pinch the skin before and while inserting the needle. This can vary from patient to patient so it is important to ask your healthcare provider if you did not receive instructions on pinching the skin. Insert the needle into the skin. Press the plunger of the syringe to inject the insulin. When you are finished injecting the insulin, pull the needle out of your skin. You may see a drop of Novolin R at the needle tip. This is normal and has no effect on the dose you just received. If you see blood after you take the needle out of your skin, press the injection site lightly with a piece of gauze or an alcohol wipe. Do not rub the area.

14. After your injection, do not recap the needle. Place used syringes, needles and used insulin vials in a disposable puncture-resistant sharps container, or some type of hard plastic or metal container with a screw on cap such as a detergent bottle or coffee can.

15. Ask your healthcare provider about the right way to throw away used syringes and needles. There may be state or local laws about the right way to throw away used syringes and needles. Do not throw away used needles and syringes in household trash or recycle.

How should I mix Novolin R with NPH insulin?

Different insulins should be mixed only under instruction from a healthcare provider. Do not mix

Novolin R should be mixed with NPH insulin right before use. When you are mixing Novolin R insulin with NPH insulin, always Novolin R with any other type of insulin except NPH insulin. draw the Novolin R (clear) insulin into the syringe first.

1. Add together the total number of units of NPH and Novolin R that you need to inject. Your total dose of medicine to inject will be the amount of NPH and Novolin R in the syringe after drawing up both insulins. For example, if you need 5 units of NPH and 2 units of Novolin R, the total dose of insulin in

the syringe would be 7 units.

Preparing your NPH and Novolin R insulins for injection:

2. Roll the NPH vial between your hands until all of the liquid in the vial is cloudy.

3. Pull the plunger of the syringe down so that the dark end is lined up to the number of units needed for your NPH insulin. This will draw into the syringe the same amount of air as the NPH dose needed.

4. Put the needle through the rubber stopper of the cloudy NPH insulin bottle. After you inject the air into the NPH vial, remove the needle from the vial but do not withdraw any of the NPH insulin. Putting air in the bottle makes it easier to draw the insulin out of the bottle.

5. Pull the plunger of the syringe down to the number of units needed for your Novolin R insulin. After you draw the air into the syringe, inject the air into the Novolin R vial.

Drawing up and mixing your NPH and Novolin R insulins for injection:

6. With the needle in place, turn the clear insulin vial of Novolin R upside down and slowly pull the plunger back to a few units beyond the right dose of Novolin R. The tip of the needle must be in the Novolin R liquid to get the full dose and not an air dose.

7. Check the syringe for air bubbles. If you see air bubbles, tap the syringe gently with your finger to

raise the air bubbles to the top. Then slowly push the plunger to the marking for your correct dose. This process should move any air bubbles in the syringe back into the vial.

8. After withdrawing the needle from the Novolin R vial, insert the needle into the NPH vial.

9. Turn the NPH vial upside down with the syringe and needle still in the vial. Slowly pull the plunger back to withdraw your NPH dose.

Remember the total dose of medicine in the syringe should be your total dose of NPH and Novolin R insulins. (See Step 1 under “How should I mix Novolin R with NPH insulin?”)

10. Inject your insulin right away otherwise it might not work properly.

This Patient Instructions for Use has been approved by the Food and Drug Administration.

Date of Issue: 03/2013

Novolin is a registered trademark of Novo Nordisk A/S.®

© 2002-2013 Novo Nordisk

Manufactured by:

Novo Nordisk A/S

DK-2880 Bagsvaerd, Denmark

For information about Novolin R contact:

Novo Nordisk Inc.

800 Scudders Mill Road

Plainsboro, New Jersey 08536

1-800-727-6500

www.novonordisk-us.com